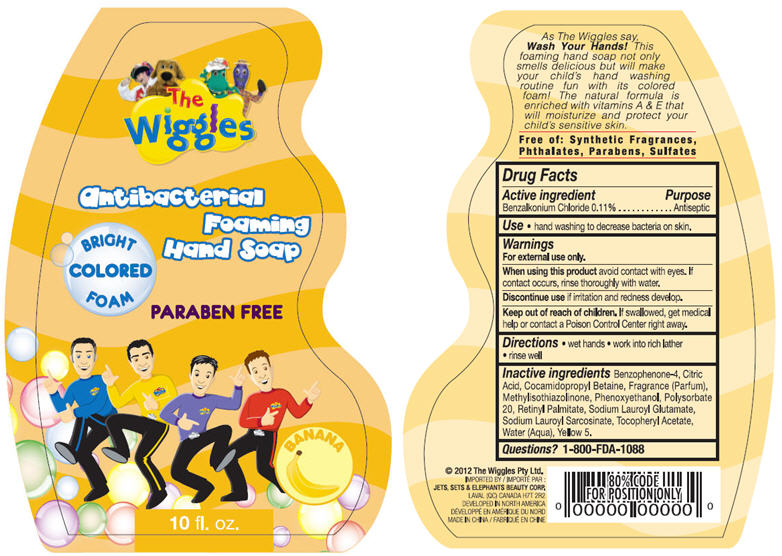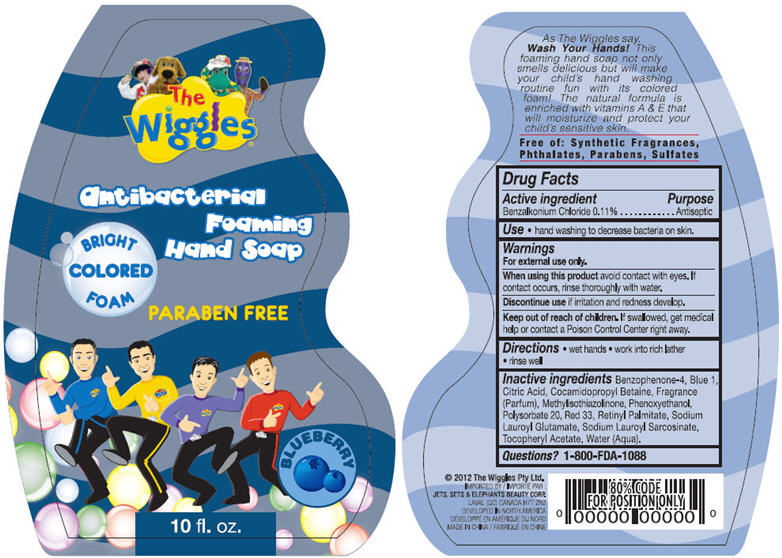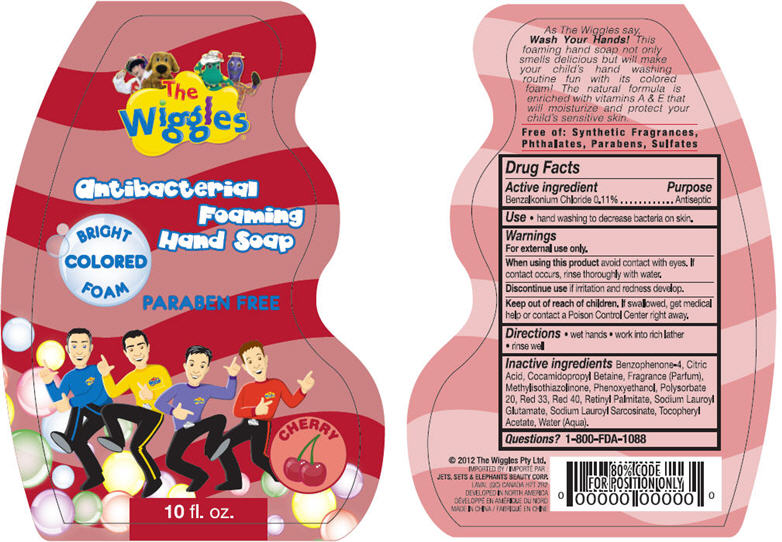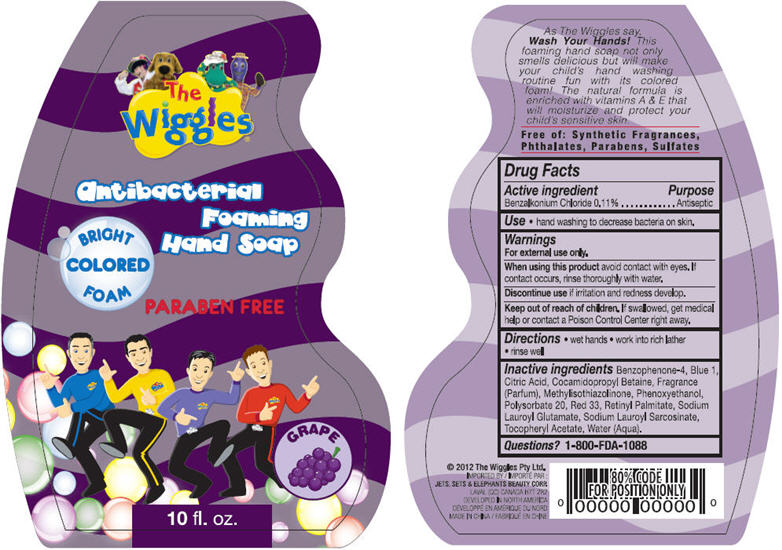 DRUG LABEL: Antibacterial Foaming Hand
NDC: 50988-290 | Form: SOLUTION
Manufacturer: Jets, Sets, & Elephants Beauty Corp.
Category: otc | Type: HUMAN OTC DRUG LABEL
Date: 20120123

ACTIVE INGREDIENTS: BENZALKONIUM CHLORIDE 0.325 mL/295.74 mL
INACTIVE INGREDIENTS: SULISOBENZONE; CITRIC ACID MONOHYDRATE; COCAMIDOPROPYL BETAINE; METHYLISOTHIAZOLINONE; PHENOXYETHANOL; POLYSORBATE 20; VITAMIN A PALMITATE; SODIUM LAUROYL GLUTAMATE; SODIUM LAUROYL SARCOSINATE; .ALPHA.-TOCOPHEROL ACETATE, D-; WATER; FD&C YELLOW NO. 5

The Wiggles® Antibacterial Foaming Hand Soap - Banana, Blueberry, Cherry, Grape

Active ingredient

Benzalkonium Chloride 0.11%

Purpose

Antiseptic

Use

- hand washing to decrease bacteria on skin.

Warnings

For external use only.

When using this product avoid contact with eyes. If contact occurs, rinse thoroughly with water.

Discontinue use if irritation and redness develop.

Keep Out of Reach of Children.

If swallowed, get medical help or contact a Poison Control Center right away.

Directions

- wet hands
- work into rich lather
- rinse well

Inactive ingredients

Banana

Benzophenone-4, Citric Acid, Cocamidopropyl Betaine, Parfum, Methylisothiazolinone, Phenoxyethanol, Polysorbate 20, Retinyl Palmitate, Sodium Lauroyl Glutamate, Sodium Lauroyl Sarcosinate, Tocopheryl Acetate, Aqua, Yellow 5

Blueberry

Benzophenone-4, Citric Acid, Cocamidopropyl Betaine, Parfum, Methylisothiazolinone, Phenoxyethanol, Polysorbate 20, Retinyl Palmitate, Sodium Lauroyl Glutamate, Sodium Lauroyl Sarcosinate, Tocopheryl Acetate, Aqua, Blue 1, Red 33

Cherry

Benzophenone-4, Citric Acid, Cocamidopropyl Betaine, Parfum, Methylisothiazolinone, Phenoxyethanol, Polysorbate 20, Retinyl Palmitate, Sodium Lauroyl Glutamate, Sodium Lauroyl Sarcosinate, Tocopheryl Acetate, Aqua, Red 33, Red 40

Grape

Benzophenone-4, Citric Acid, Cocamidopropyl Betaine, Parfum, Methylisothiazolinone, Phenoxyethanol, Polysorbate 20, Retinyl Palmitate, Sodium Lauroyl Glutamate, Sodium Lauroyl Sarcosinate, Tocopheryl Acetate, Aqua, Blue 1, Red 33

Questions?

1-800-FDA-1088

©2012 The Wiggles Pty Ltd.

IMPORTED BY:

JETS, SETS, & ELEPHANTS BEAUTY CORP.

LAVAL (QC) CANADA H7T 2R2

DEVELOPED IN NORTH AMERICA

MADE IN CHINA

Principal Display Panel - Bottle Label

The Wiggles®

Antibacterial

Foaming

Hand Soap

BRIGHT COLORED FOAM

PARABEN FREE

BANANA

10 fl. oz.

As The Wiggles say,
Wash Your Hands! This
foaming hand soap not only
smells delicious but will make
your child's hand washing
routine fun with its colored
foam! The natural formula is
enriched with vitamins A & E that
will moisturize and protect your
child's sensitive skin.

Free of: Synthetic Fragrances,
Phthalates, Parabens, Sulfates

Banana Bottle Label

Principal Display Panel - Bottle Label

The Wiggles®

Antibacterial

Foaming

Hand Soap

BRIGHT COLORED FOAM

PARABEN FREE

BLUEBERRY

10 fl. oz.

As The Wiggles say,
Wash Your Hands! This
foaming hand soap not only
smells delicious but will make
your child's hand washing
routine fun with its colored
foam! The natural formula is
enriched with vitamins A & E that
will moisturize and protect your
child's sensitive skin.

Free of: Synthetic Fragrances,
Phthalates, Parabens, Sulfates

Blueberry Bottle Label

Principal Display Panel - Bottle Label

The Wiggles®

Antibacterial

Foaming

Hand Soap

BRIGHT COLORED FOAM

PARABEN FREE

CHERRY

10 fl. oz.

As The Wiggles say,
Wash Your Hands! This
foaming hand soap not only
smells delicious but will make
your child's hand washing
routine fun with its colored
foam! The natural formula is
enriched with vitamins A & E that
will moisturize and protect your
child's sensitive skin.

Free of: Synthetic Fragrances,
Phthalates, Parabens, Sulfates

Cherry Bottle Label

Principal Display Panel - Bottle Label

The Wiggles®

Antibacterial

Foaming

Hand Soap

BRIGHT COLORED FOAM

PARABEN FREE

GRAPE

10 fl. oz.

As The Wiggles say,
Wash Your Hands! This
foaming hand soap not only
smells delicious but will make
your child's hand washing
routine fun with its colored
foam! The natural formula is
enriched with vitamins A & E that
will moisturize and protect your
child's sensitive skin.

Free of: Synthetic Fragrances,
Phthalates, Parabens, Sulfates

Grape Bottle Label